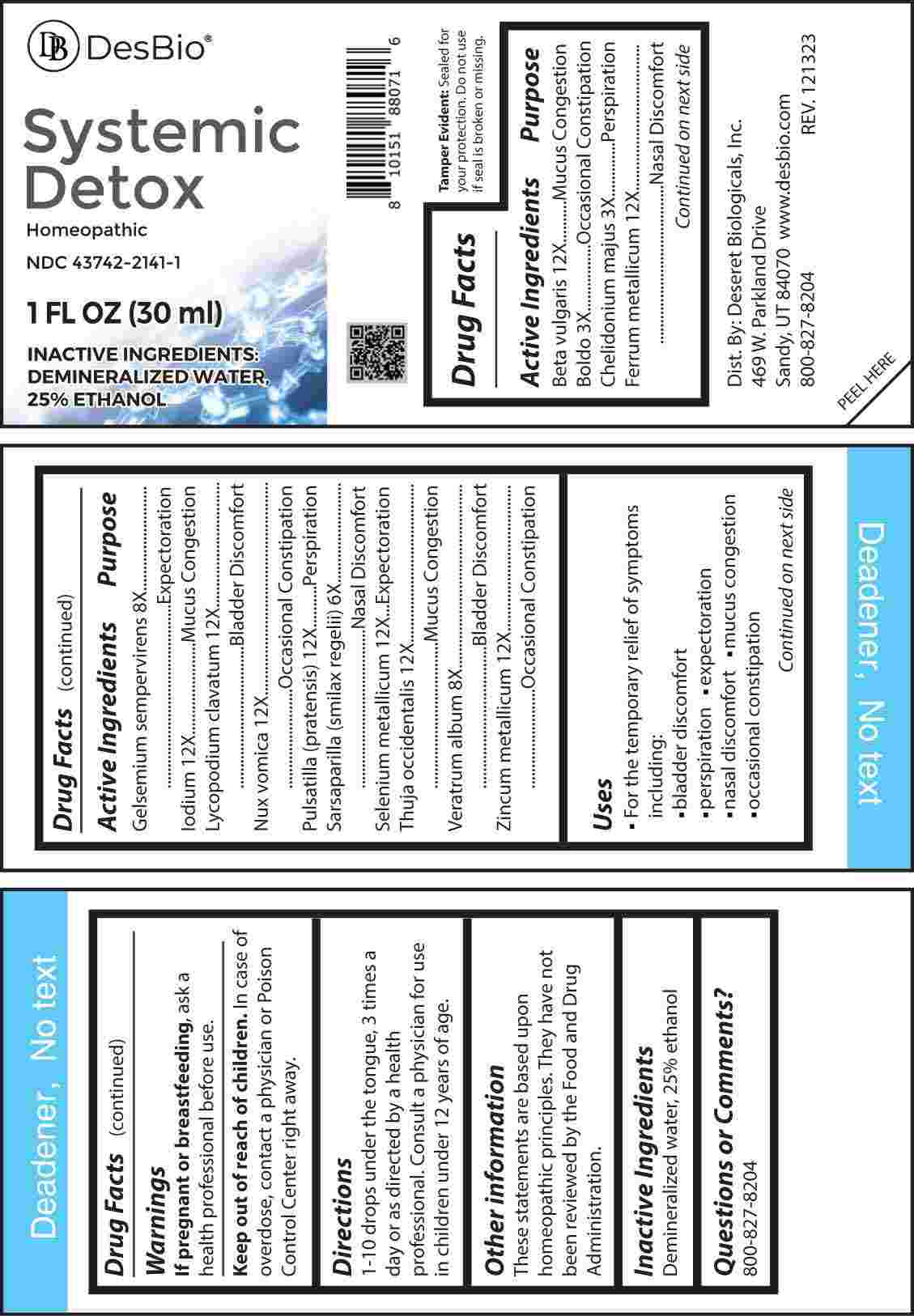 DRUG LABEL: Systemic Detox
NDC: 43742-2141 | Form: LIQUID
Manufacturer: Deseret Biologicals, Inc.
Category: homeopathic | Type: HUMAN OTC DRUG LABEL
Date: 20240313

ACTIVE INGREDIENTS: BETA VULGARIS WHOLE 12 [hp_X]/1 mL; PEUMUS BOLDUS LEAF 3 [hp_X]/1 mL; CHELIDONIUM MAJUS WHOLE 3 [hp_X]/1 mL; IRON 12 [hp_X]/1 mL; GELSEMIUM SEMPERVIRENS ROOT 8 [hp_X]/1 mL; IODINE 12 [hp_X]/1 mL; LYCOPODIUM CLAVATUM SPORE 12 [hp_X]/1 mL; STRYCHNOS NUX-VOMICA SEED 12 [hp_X]/1 mL; PULSATILLA PRATENSIS WHOLE 12 [hp_X]/1 mL; SMILAX ORNATA ROOT 6 [hp_X]/1 mL; SELENIUM 12 [hp_X]/1 mL; THUJA OCCIDENTALIS LEAFY TWIG 12 [hp_X]/1 mL; VERATRUM ALBUM ROOT 8 [hp_X]/1 mL; ZINC 12 [hp_X]/1 mL
INACTIVE INGREDIENTS: WATER; ALCOHOL

DRUG FACTS:

ACTIVE INGREDIENTS:

Beta Vulgaris 12X, Boldo 3X, Chelidonium Majus 3X, Ferrum Metallicum 12X, Gelsemium Sempervirens 8X, Iodium 12X, Lycopodium Clavatum 12X, Nux Vomica 12X, Pulsatilla (Pratensis) 12X, Sarsaparilla (Smilax Regelii) 6X, Selenium Metallicum 12X, Thuja Occidentalis 12X, Veratrum Album 8X, Zincum Metallicum 12X.

PURPOSE:

Beta Vulgaris – Mucus Congestion, Boldo – Occasional Constipation, Chelidonium Majus - Perspiration, Ferrum Metallicum – Nasal Discomfort, Gelsemium Sempervirens - Expectoration, Iodium – Mucus Congestion, Lycopodium Clavatum – Bladder Discomfort, Nux Vomica – Occasional Constipation, Pulsatilla (Pratensis) - Perspiration, Sarsaparilla (Smilax Regelii) – Nasal Discomfort, Selenium Metallicum - Expectoration, Thuja Occidentalis – Mucus Congestion, Veratrum Album – Bladder Discomfort, Zincum Metallicum – Occasional Constipation

USES:

• For the temporary relief of symptoms including:

• bladder discomfort

• perspiration • expectoration

• nasal discomfort • mucus congestion

• occasional constipation

These statements are based upon homeopathic principles. They have not been reviewed by the Food and Drug Administration.

WARNINGS:

If pregnant or breast-feeding, ask a health professional before use.

Keep out of reach of children. In case of overdose, contact a physician or Poison Control Center right away.

Tamper Evident: Sealed for your protection. Do not use if seal is broken or missing.

KEEP OUT OF REACH OF CHILDREN:

In case of overdose, contact a physician or Poison Control Center right away.

DIRECTIONS:

1-10 drops under the tongue, 3 times a day or as directed by a health professional. Consult a physician for use in children under 12 years of age.

INACTIVE INGREDIENTS:

Demineralized water, 25% ethanol

QUESTIONS:

Dist. By: Deseret Biologicals, Inc.

469 W. Parkland Drive

Sandy, UT 84070

www.desbio.com

800-827-8204

PACKAGE LABEL DISPLAY:

DesBio

Systemic Detox

Homeopathic

NDC 43742-2141-1

1 FL OZ (30 ml)